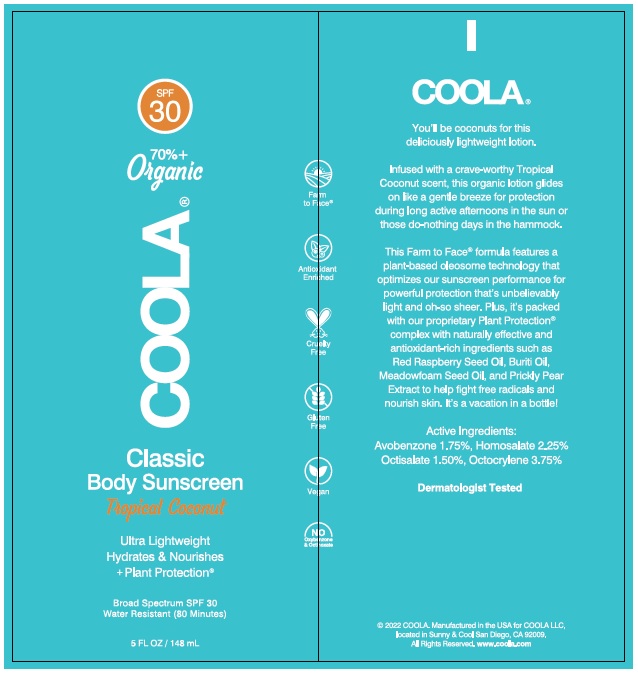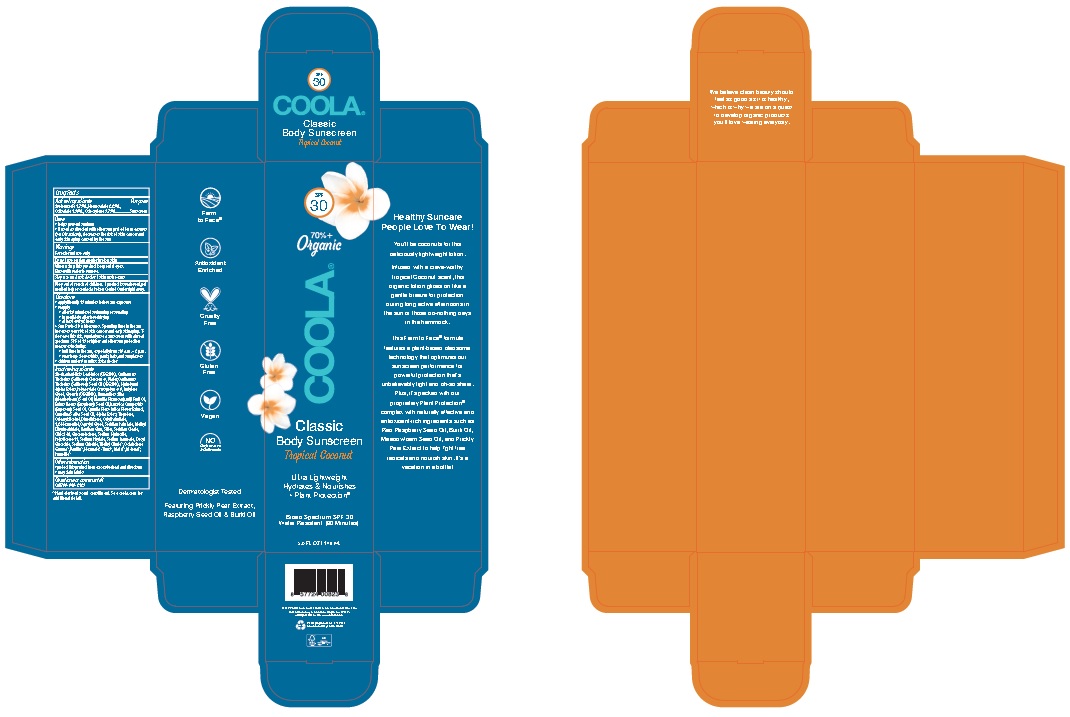 DRUG LABEL: COOLA Classic Body Sunscreen Tropical Coconut
NDC: 79753-076 | Form: LOTION
Manufacturer: COOLA LLC
Category: otc | Type: HUMAN OTC DRUG LABEL
Date: 20241227

ACTIVE INGREDIENTS: OCTISALATE 15 mg/1 mL; OCTOCRYLENE 37.5 mg/1 mL; HOMOSALATE 22.5 mg/1 mL; AVOBENZONE 17.5 mg/1 mL
INACTIVE INGREDIENTS: SODIUM HYDROXIDE; XANTHAN GUM; WATER; TROPOLONE; PHYTATE SODIUM; ALOE VERA LEAF; DECYL GLUCOSIDE; CITRIC ACID MONOHYDRATE; BUTYLENE GLYCOL; ALCOHOL; 1,2-HEXANEDIOL; PHENOXYETHANOL; METHYL DIHYDROABIETATE; SODIUM BENZOATE; RASPBERRY SEED OIL; DIMETHICONE/VINYL DIMETHICONE CROSSPOLYMER (SOFT PARTICLE); TOCOPHEROL; TERT-BUTYL ALCOHOL; SODIUM CHLORIDE; SILICON DIOXIDE; AMMONIUM ACRYLOYLDIMETHYLTAURATE, DIMETHYLACRYLAMIDE, LAURYL METHACRYLATE AND LAURETH-4 METHACRYLATE COPOLYMER, TRIMETHYLOLPROPANE TRIACRYLATE CROSSLINKED (45000 MPA.S); OPUNTIA FICUS-INDICA; JOJOBA OIL, RANDOMIZED; HYDROGENATED JOJOBA OIL, RANDOMIZED; HEXYLENE GLYCOL; GLUCONOLACTONE; CARTHAMUS TINCTORIUS SEEDCAKE; DIMETHICONE; MAURITIA FLEXUOSA FRUIT OIL; MEADOWFOAM SEED OIL; GLYCERIN; SAFFLOWER OIL; CAPRYLYL GLYCOL; CAMELINA SATIVA SEED OIL; CANOLA OIL; CARTHAMUS TINCTORIUS (SAFFLOWER) OLEOSOMES

COOLA Classic Body Sunscreen Tropical Coconut SPF 30

Active Ingredients

AVOBENZONE 1.75%, HOMOSALATE 2.25%, OCTISALATE 1.5%, OCTOCRYLENE 3.75%

PURPOSE

Sunscreen

Uses

* helps prevent sunburn

* if used as directed with other sun protection measures (see Directions), decreases the risk of skin cancer and early skin aging caused by the sun

Warnings

For external use only

Do not use on damaged or broken skin

When using this product keep out of eyes. Rinse with water to remove

Stop use and ask doctor if skin rash occurs

Keep out of reach of children. If product is swallowed, get medical help or contact a Poison Control Center right away.

Directions

* apply liberally 15 minutes before sun exposure

* reapply:

* after 80 minutes of swimming or sweating

* immediately after towel drying

* at least every 2 hours

* Sun Protection Measures. Spending time in the sun increases your risk of skin cancer and early aging. To decrease this risk, regularly use a sunscreen with a broad spectrum SPF of 15 or higher and other sun protection measures including:
* limit time in the sun, especially from: 10 a.m. – 2 p.m.
* wear long-sleve shirts, pants, hats, and sunglasses

* children under 6 months: Ask a doctor

Inactive ingredients

Aloe Barbadensis Leaf Juice (ORGANIC), Brassica Campestris (Rapeseed) Seed Oil, Butylene Glycol, Camelina Sativa Seed Oil, Caprylyl Glycol, Carthamus Tinctorius (Safflower) Oleosomes, Carthamus Tinctorius (ORGANIC Safflower) Seed Oil, Carthamus Tinctorius (Safflower) Seedcake Extract, Decyl Glucoside, Dimethicone, Gamma-Nonalactone, Glycerin (ORGANIC), Hydrogenated Methyl Abietata, Hydrolyzed Jojoba Esters, Jojoba Esters, Limnanthes Alba (Meadowfoam) Seed Oil, Mauritia Flexuosa Fruit Oil, 1,2 Hexanediol, Opuntia Ficus-Indica Flower Extract, Polyacrylate Crosspolymer-6, Polysilicone-11, Rubus Idaeus (Raspberry) Seed Oil, Silica, Sodium Phytate, Tropolone, Vanillin, Xanthan Gum

Other Information

* protect this product from excessive heat and direct sun

Questions or comments? Call 760-940-2125

Product Labeling

COOLA

Classic
Body Sunscreen

Tropical Coconut

Broad Spectrum SPF 30
Water Resistant (80 Minutes)

5.0 FL OZ / 148 mL

© 2022 COOLA. Manufactured in the USA for COOLA LLC,
located in Sunny & Cool San Diego, CA 92009.
All Rights Reserved. www.coola.com

res